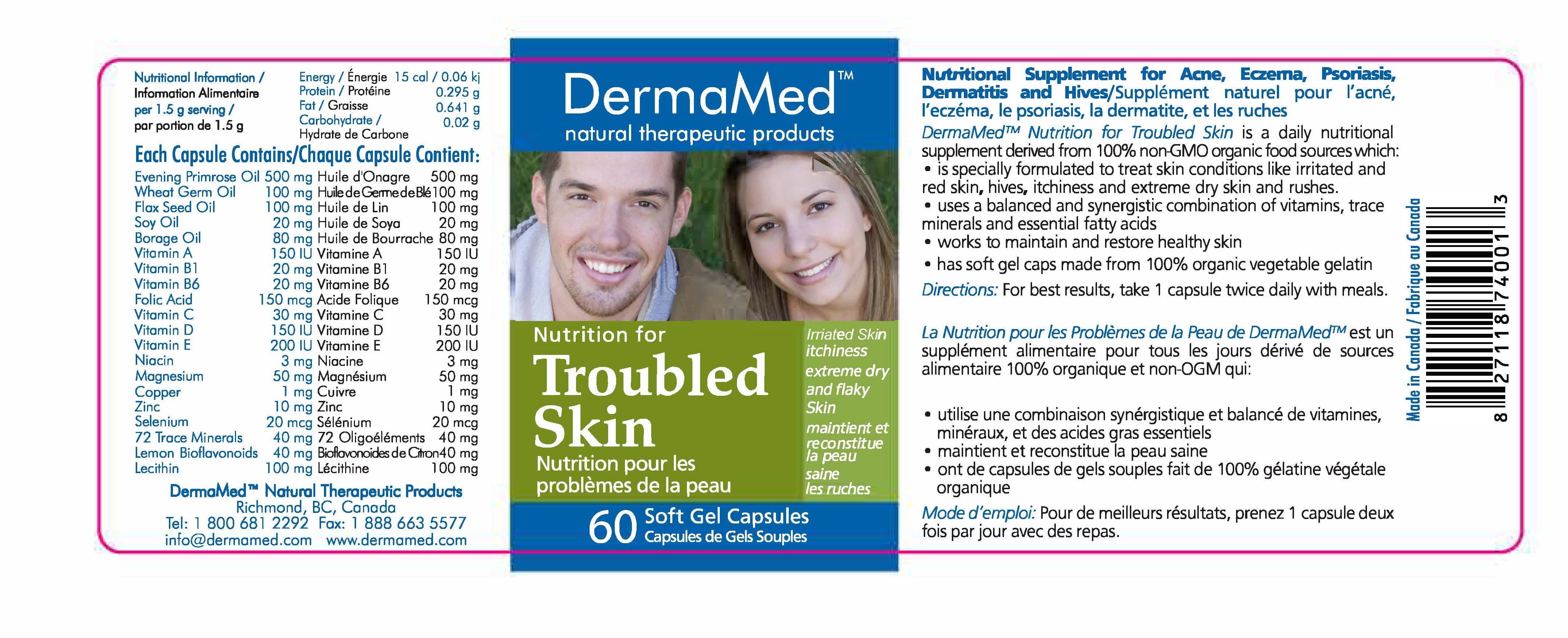 DRUG LABEL: Dermamed Nutrition for troubled skin
NDC: 69711-687 | Form: CAPSULE, GELATIN COATED
Manufacturer: DermaMed
Category: otc | Type: HUMAN OTC DRUG LABEL
Date: 20190918

ACTIVE INGREDIENTS: VITAMIN D 150 [iU]/1.5 g; MAGNESIUM ASPARTATE 50 mg/1.5 g; ZINC GLUCONATE 10 mg/1.5 g; THIAMINE 20 mg/1.5 g; COPPER CU-64 1 mg/1.5 g; ASCORBIC ACID 30 mg/1.5 g; VITAMIN A 150 [iU]/1.5 g
INACTIVE INGREDIENTS: NIACIN 3 mg/1.5 g; PYRIDOXAL 20 mg/1.5 g; FOLIC ACID 150 ug/1.5 g; CITRUS BIOFLAVONOIDS 40 mg/1.5 g; LECITHIN, SUNFLOWER 100 mg/1.5 g; EVENING PRIMROSE OIL 500 mg/1.5 g; WHEAT GERM OIL 100 mg/1.5 g; FLAX SEED 100 mg/1.5 g; SOYBEAN OIL 20 mg/1.5 g; BORAGE OIL 80 mg/1.5 g; SELENIUM CHLORIDE 20 mg/1.5 g

DermaMed Natural theropeutic products

PACKAGE LABEL

PURPOSE

Nutritional Supplement for Acne, Eczema, Psoriasis,
Dermatitis and Hives/Supplement naturel pour l'acne,
I' eczema, le psoriasis, la dermatite, et !es ruches
DermaMed™ Nutrition for Troubled Skin is a daily nutritional
supplement derived from 100"/4 non-<:iMO organic food sources which:
• is specially formulated to treat skin conditions like irritated and
red skin, hives, itchiness and extreme dry skin and rushes.
• uses a balanced and synergistic combination of vitamins, trace
minerals and essential fatty acids
• works to maintain and restore healthy skin
• has soft gel caps made from 100% organic vegetable gelatin

DESCRIPTION

Nutritional Supplement for Acne, Eczema, Psoriasis,
Dermatitis and Hives/Supplement naturel pour l'acne,
I' eczema, le psoriasis, la dermatite, et !es ruches
DermaMed™ Nutrition for Troubled Skin is a daily nutritional
supplement derived from 100"/4 non-<:iMO organic food sources which:
• is specially formulated to treat skin conditions like irritated and
red skin, hives, itchiness and extreme dry skin and rushes.
• uses a balanced and synergistic combination of vitamins, trace
minerals and essential fatty acids
• works to maintain and restore healthy skin
• has soft gel caps made from 100% organic vegetable gelatin

Indication and usage

Nutritional Supplement for Acne, Eczema, Psoriasis,
Dermatitis and Hives/DermaMed™ Nutrition for Troubled Skin is a daily nutritional
supplement derived from 100"/4 non-<:iMO organic food sources which:
• is specially formulated to treat skin conditions like irritated and
red skin, hives, itchiness and extreme dry skin and rushes.
• uses a balanced and synergistic combination of vitamins, trace
minerals and essential fatty acids
• works to maintain and restore healthy skin
• has soft gel caps made from 100% organic vegetable gelatin
Directions: For best results, take 1 capsule twice daily with meals

ACTIVE INGREDIENT

Each capsule contains:

Evening Primrose Oil 500 mg Huile d'Onagre 500 mg
Wheat Gem1 Oil l 00 mg HIM! de Genre de Biel 00 mg
Flax Seed Oil l 00 mg Huile de Lin 100 mg
Soy Oil 20 mg Huile de Soya 20 mg
Borage Oil 80 mg Huile de Bourrache 80 mg
Vitomin A 150 IU Vitamine A 150 IU
Vitamin Bl 20 mg Vita mine Bl 20 mg
Vitamin B6 20 mg Vrlamine B6 20 mg
Folic Acid 150 mcg Acide Folique 150 mcg
Vitamin C 30 mg Vitamine C 30 mg
Vitamin D 150 IU Vitamine D 150 IU
Vitamin E 200 IU Vrlamine E 200 IU
Niacin 3 mg Niacine 3 mg
Magnesium 50 mg Magnesium 50 mg
Copper 1 mg Cuivre 1 mg
Zinc 10 mg Zinc 10 mg
Selenium 20 mcg Selenium 20 mcg
72 Trace Minerals 40 mg 72 Oligoelements 40 mg
lemon Bioflavonoids 40 mg Biclb.onoidesde0on40 mg
lecithin 100 mg l.ecithine 100 mg

Dosage

DermaMed™ Nutrition for Troubled Skin is a daily nutritional
supplement derived from 100"/4 non-<:iMO organic food sources which:
• is specially formulated to treat skin conditions like irritated and
red skin, hives, itchiness and extreme dry skin and rushes.
• uses a balanced and synergistic combination of vitamins, trace
minerals and essential fatty acids
• works to maintain and restore healthy skin
• has soft gel caps made from 100% organic vegetable gelatin
Directions: For best results, take 1 capsule twice daily with meals

1.5 g per serving

WARNINGS AND PRECAUTIONS

For best results, take 1 capsule twice daily with meals

BOXED WARNING

For best results, take 1 capsule twice daily with meals

** Keep out of reach of children